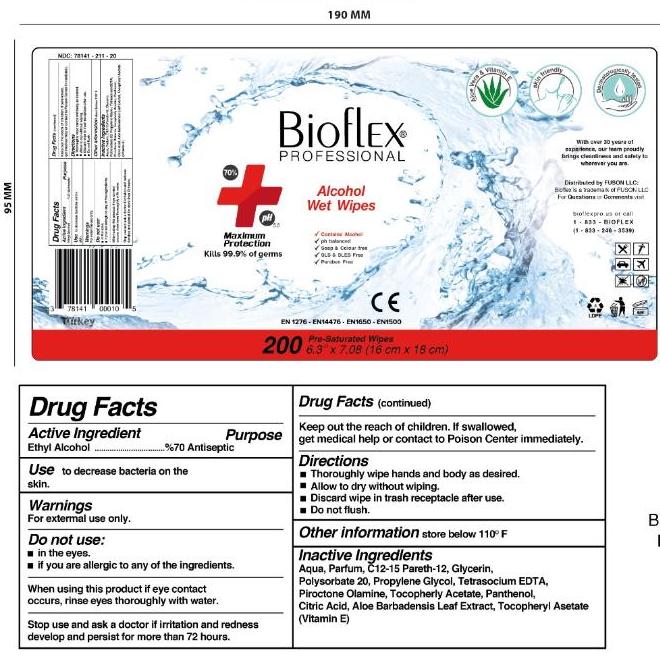 DRUG LABEL: Alcohol Hand Wipes
NDC: 78141-211 | Form: CLOTH
Manufacturer: Fuson LLC
Category: otc | Type: HUMAN OTC DRUG LABEL
Date: 20200821

ACTIVE INGREDIENTS: ALCOHOL 3.059 mL/4.37 mL
INACTIVE INGREDIENTS: DEXPANTHENOL; PEG-7 GLYCERYL COCOATE; EDETIC ACID; ANHYDROUS CITRIC ACID; WATER; POLYSORBATE 20; COCAMIDOPROPYL BETAINE; LEMON OIL, DISTILLED; GLYCERIN

Active Ingredient

Ethyl Alcohol (Ethanol) 70%

Inactive Ingredients

Aqua, glycerin, peg-7 glyceryl cocoate, polysorbate 20, cocamidopropyl betaine, dexpanthenol, citrus limon peel, citric acid, EDTA

Purpose

Antiseptic- Antibacterial hand towelettes

Use

Wipes used on hands and skin to reduce bacteria

Warnings

For external use only, do not ingest. Do not use near eyes. Keep away from flame and direct sunlight. Do not eat, drink, or smoke during use. If irritation or redness occurs and persists for longer than 72 hours, consult a medical professional.

Do not use near eyes. Do not ingest. Do not eat, smoke, or drink during use. Do not use on or in open skin wounds. Do not use on children under 2 months of age.

When Using

If ingested, contact a poison control center immediately. If eye contact occurs, flush eyes with water repeatidly.

Stop Use

Stop use if redness, irritation, or rash occurs.

KEEP OUT OF REACH OF CHILDREN

Store in places out of reach of children. Supervise use by children under the age of 6.

Dierctions

Peel back open label slowly. Pull out one wipe at a time and re-seal the packaging tightly. Wet hands thoroughly with product and allow to dry without wiping.

Storage

Keep away from direct sunlight. Store tightly closed in its original packaging and in a cool, dry place. Keep away from food, drinks, and animal feed. Store away from reach of children.

Package Label

120 Count Canister: 78141-211-12

200 Count Canister: 78141-211-20

500 Count Canister: 78141-211-50